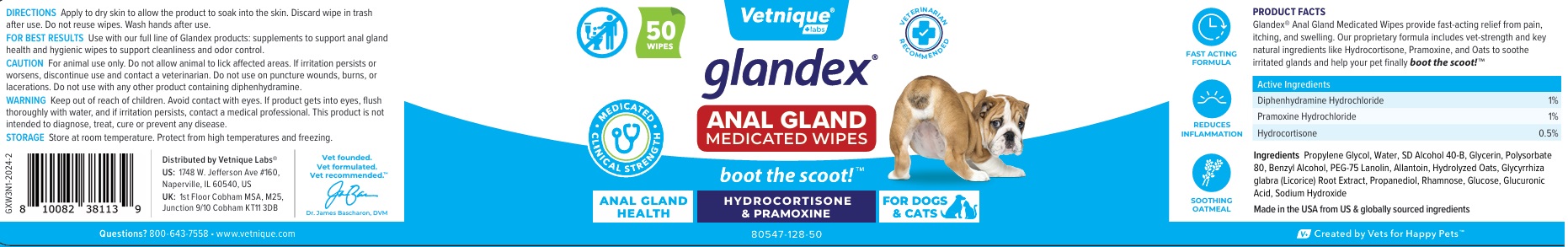 DRUG LABEL: glandex ANAL GLAND MEDICATED WIPES
NDC: 80547-128 | Form: CLOTH
Manufacturer: Vetnique Labs LLC
Category: animal | Type: OTC ANIMAL DRUG LABEL
Date: 20241028

ACTIVE INGREDIENTS: DIPHENHYDRAMINE HYDROCHLORIDE 10 mg/1 mL; PRAMOXINE HYDROCHLORIDE 10 mg/1 mL; HYDROCORTISONE 5 mg/1 mL
INACTIVE INGREDIENTS: PROPYLENE GLYCOL; WATER; ALCOHOL; GLYCERIN; POLYSORBATE 80; BENZYL ALCOHOL; PEG-75 LANOLIN; ALLANTOIN; OAT; GLYCYRRHIZA GLABRA; PROPANEDIOL; RHAMNOSE; ANHYDROUS DEXTROSE; GLUCURONIC ACID; SODIUM HYDROXIDE

glandex® ANAL GLAND MEDICATED WIPES

PRODUCT FACTS

Glandex® Anal Gland Medicated Wipes provide fast-acting relief from pain, itching, and swelling. Our proprietary formula includes vet-strength and key natural ingredients like Hydrocortisone, Pramoxine, and Oats to soothe irritated glands and help your pet finally boot the scoot!™

Active Ingredients

Diphenhydramine Hydrochloride 1%
Pramoxine Hydrochloride 1%
Hydrocortisone 0.5%

Ingredients

Propylene Glycol, Water, SD Alcohol 40-B, Glycerin, Polysorbate 80, Benzyl Alcohol, PEG-75 Lanolin, Allantoin, Hydrolyzed Oats, Glycyrrhiza glabra (Licorice) Root Extract, Propanediol, Rhamnose, Glucose, Glucuronic Acid, Sodium Hydroxide

DIRECTIONS

Apply to dry skin to allow the product to soak into the skin. Discard wipe in trash after use. Do not reuse wipes. Wash hands after use.

FOR BEST RESULTS Use with our full line of Glandex products: supplements to support anal gland health and hygienic wipes to support cleanliness and odor control.

CAUTION

For animal use only. Do not allow animal to lick affected areas. If irritation persists or worsens, discontinue use and contact a veterinarian. Do not use on puncture wounds, burns, or lacerations. Do not use with any other product containing diphenhydramine.

WARNING

Keep out of reach of children. Avoid contact with eyes. If product gets into eyes, flush thoroughly with water, and if irritation persists, contact a medical professional. This product is not intended to diagnose, treat, cure or prevent any disease.

STORAGE

Store at room temperature. Protect from high temperatures and freezing.

VETERINARIAN RECOMMENDED

• MEDICATED • CLINICAL STRENGTH

ANAL GLAND HEALTH

HYDROCORTISONE & PRAMOXINE

FOR DOGS & CATS

FAST ACTING FORMULA

REDUCES INFLAMMATION

SOOTHING OATMEAL

Made in the USA from US & globally sourced ingredients

V+ Created by Vets for Happy Pets™

Distributed by Vetnique Labs®
US: 1748 W. Jefferson Ave #160,
Naperville, IL 60540, US
UK: 1st Floor Cobham MSA, M25,
Junction 9/10 Cobham KT11 3DB

Questions? 800-643-7558 • www.vetnique.com

Vet founded.
Vet formulated.
Vet recommended.™